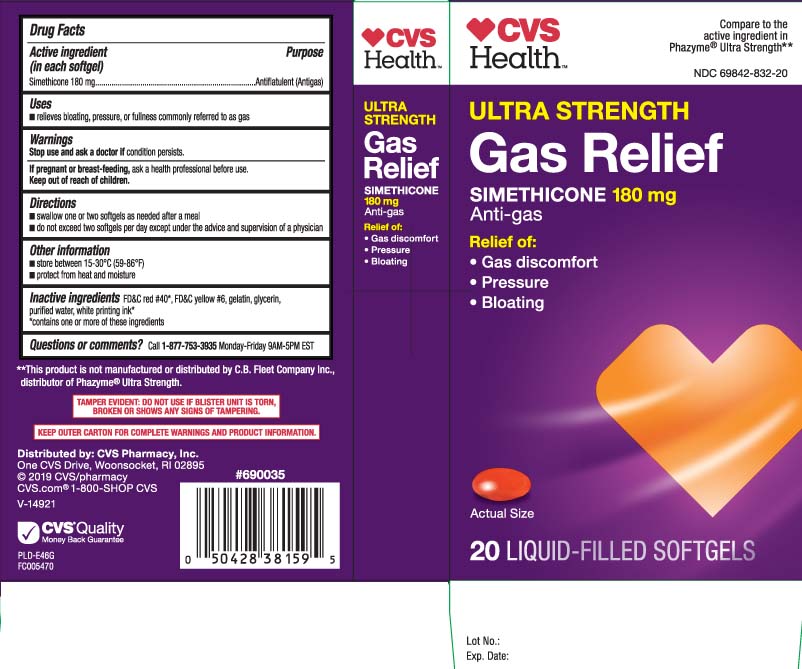 DRUG LABEL: Gas Relief
NDC: 69842-832 | Form: CAPSULE, LIQUID FILLED
Manufacturer: CVS Pharmacy
Category: otc | Type: HUMAN OTC DRUG LABEL
Date: 20240313

ACTIVE INGREDIENTS: DIMETHICONE 180 mg/1 1
INACTIVE INGREDIENTS: FD&C YELLOW NO. 6; GELATIN; GLYCERIN; WATER; FD&C RED NO. 40

Drug Facts

Active ingredient (in each softgel)

Simethicone 180 mg

Purpose

Antiflatulent (Antigas)

Uses

- relieves bloating, pressure, or fullness commonly referred to as gas

Warnings

Stop use and ask a doctor if

condition persists.

If pregnant or breast-feeding,

ask a health professional before use.

Directions

- swallow one or two softgels as needed after a meal
- do not exceed two softgels per day except under the advice and supervision of a physician

Other information

- store between 15-30ºC (59-86ºF)
- protect from heat and moisture

Inactive ingredients

FD&C red #40*, FD&C yellow #6, gelatin, glycerin, purified water, white printing ink*

*contains one or more of these ingredients

Questions or comments?

Call 1-877-753-3935 Monday-Friday 9AM-5PM EST

Principal Display Panel

Compare to the active ingredient in Phazyme® Ultra Strength**

ULTRA STRENGTH

GAS RELIEF

SIMETHICONE 180 mg

Anti-gas

Relief of:

- Gas discomfort
- Pressure
- Bloating

SOFTGEL

LIQUID-FILLED SOFTGELS

**This product is not manufactured or distributed by C.B. Fleet Company Inc., distributor of Phazyme® Ultra Strength.

TAMPER EVIDENT: DO NOT USE IF BLISTER UNIT IS TORN, BROKEN OR SHOW ANY SIGNS OF TAMPERING.

KEEP OUTER CARTON FOR COMPLETE WARNINGS AND PRODUCT INFORMATION.

Distributed by: CVS Pharmacy, Inc.

One CVS Drive, Woonsocket, RI 02895

Package Label

CVS HEALTH Ultra Strength Gas Relief